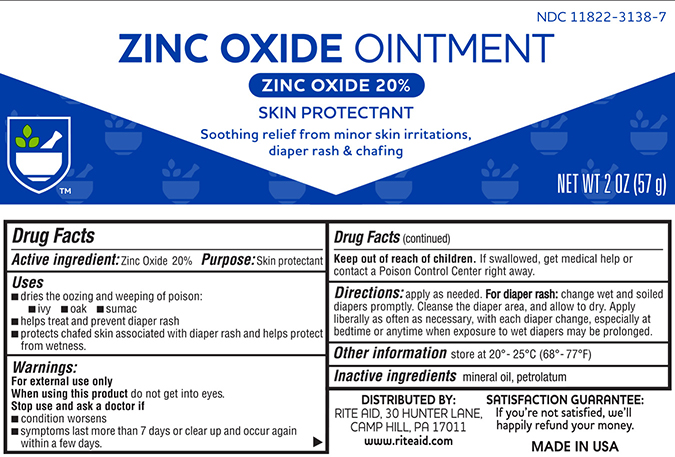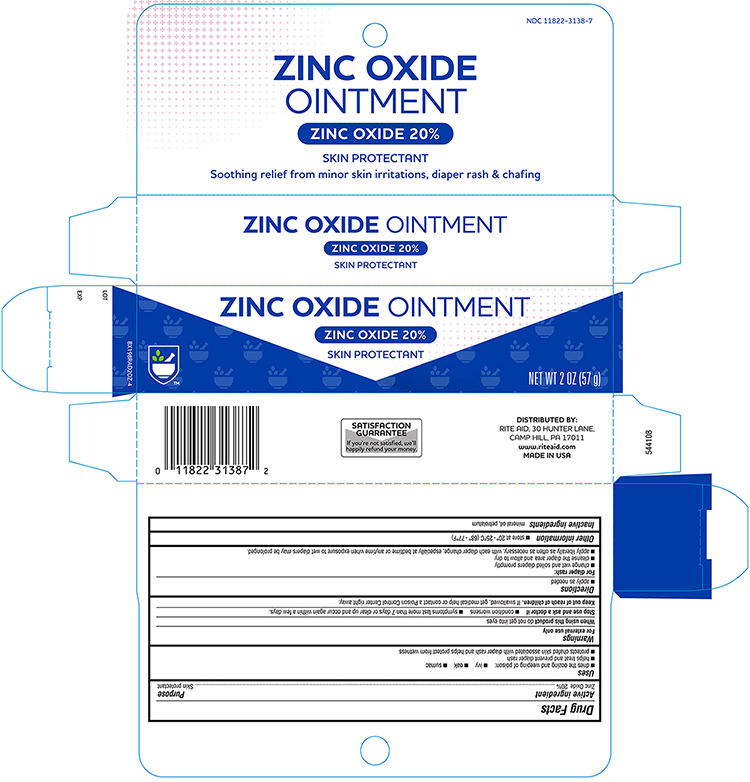 DRUG LABEL: Rite Aid  Zinc Oxide
NDC: 11822-3138 | Form: OINTMENT
Manufacturer: RITE AID
Category: otc | Type: HUMAN OTC DRUG LABEL
Date: 20241121

ACTIVE INGREDIENTS: ZINC OXIDE 200 mg/1 g
INACTIVE INGREDIENTS: MINERAL OIL; PETROLATUM

Rite Aid Zinc Oxide Ointment

Drug Facts

Active Ingredient

Zinc oxide 20%

Purpose

Skin Protectant

Uses

- helps treat and prevent diaper rash. Protects chafed skin due to diaper rash and helps seal out wetness.
- dries the oozing and weeping of poison ivy, poison oak and poison sumac.

Warnings

For external use only

When using this product, avoid contact with the eyes

Stop use and ask a doctor if

- condition worsens
- symptoms last more than 7 days to clear up and occur again within a few days

Keep out of reach of children. If swallowed, get medical help or contact a poison control center right away.

Directions

- apply liberally as often as necessary

For Diaper Rash

- change wet or soiled diapers promptly
- cleanse the diaper area and allow to dry
- apply ointment liberally, as often as necessary, with each diaper change and especially at bedtime or anytime when exposure to wet diapers may be prolonged

For Poison Ivy, poison oak and poison sumac;

- cleanse the affect area and pat dry
- apply ointment liberally, as often as necessary, using a cotton ball, sterile swab or gauze
- wash hands after use.

Inactive ingredients

mineral oil, petrolatum

Questions or comments?

Call

Store at room temperature 20 - 25°C (68° - 77°F).

Principal Display Panel – Tube

RITE AID NDC 11822-3138-7

Zinc Oxide Ointment

Zinc Oxide 20%

Skin Protectant

Soothing relief from minor skin irritations, diaper rash and chafing

Net Wt 2 OZ (57g)

Principal Display Panel – Carton

Rite Aid NDC 11822-3138-7

Zinc Oxide Ointment

Zinc Oxide 20%

Skin Protectant

Soothing Relief from minor skin irritations, diaper rash and chafing